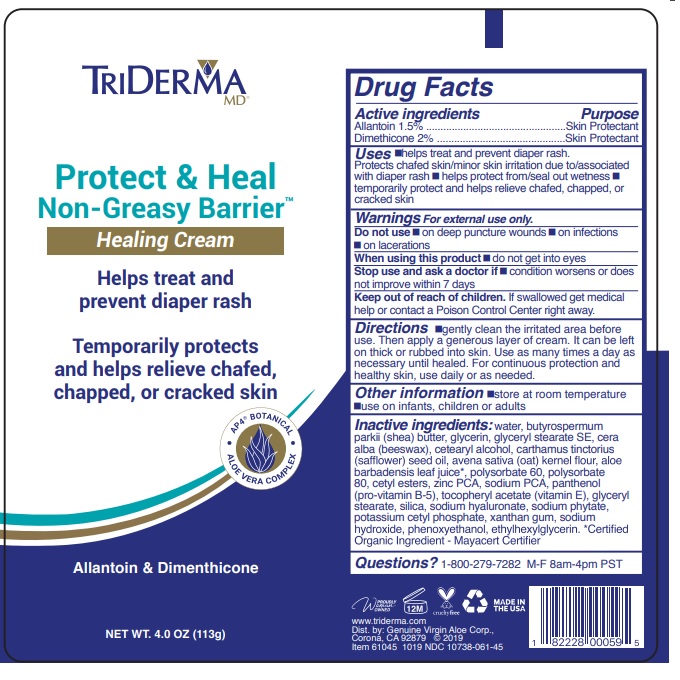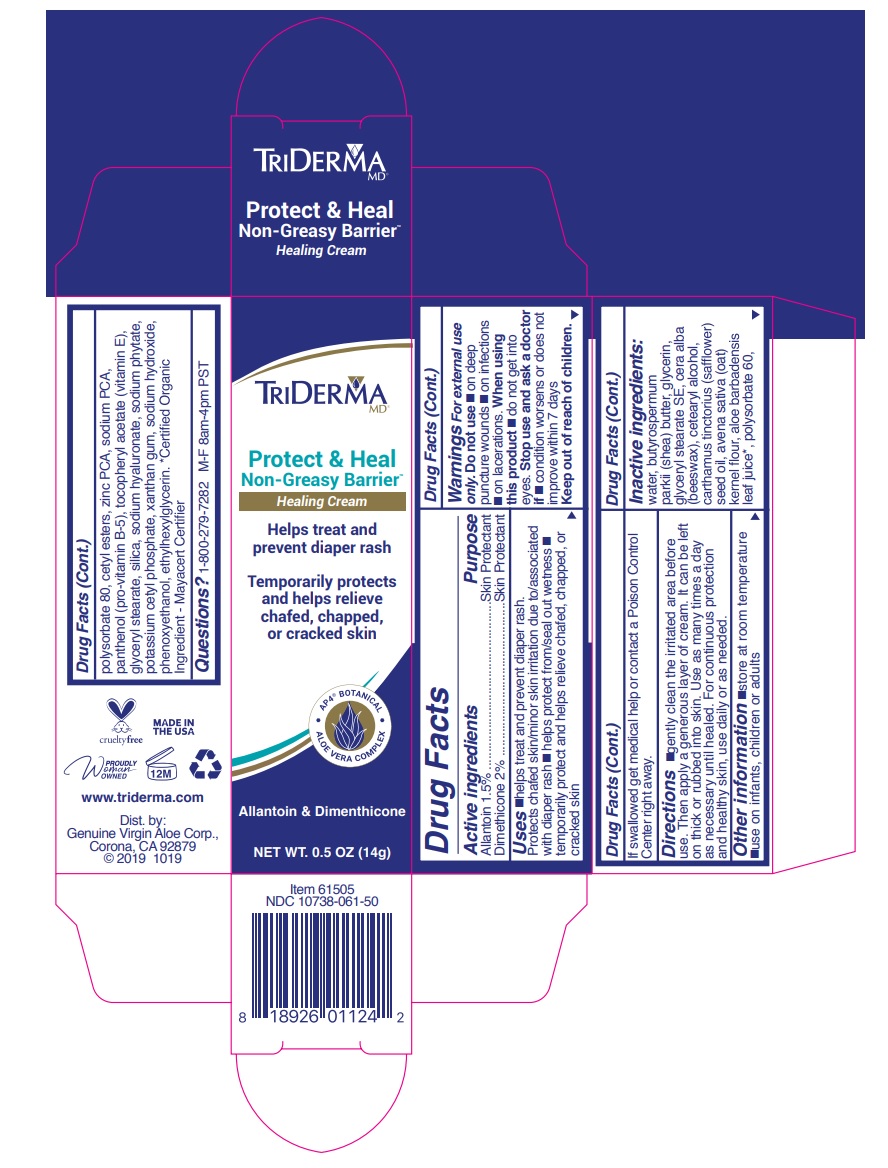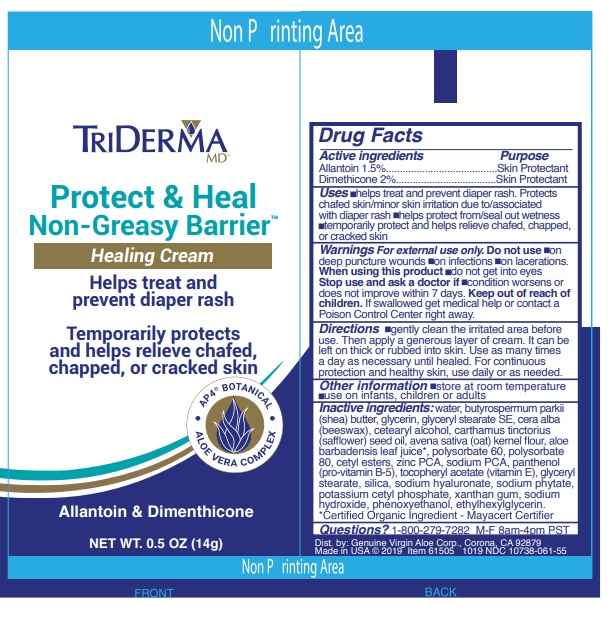 DRUG LABEL: TRIDERMA PROTECT AND HEAL NON- GREASY BARRIER
NDC: 10738-061 | Form: CREAM
Manufacturer: Genuine Virgin Aloe Corporation
Category: otc | Type: HUMAN OTC DRUG LABEL
Date: 20260128

ACTIVE INGREDIENTS: ALLANTOIN 1.5 g/100 g; DIMETHICONE 2 g/100 g
INACTIVE INGREDIENTS: WATER; SHEA BUTTER; GLYCERIN; GLYCERYL STEARATE SE; YELLOW WAX; CETOSTEARYL ALCOHOL; SAFFLOWER OIL; OATMEAL; ALOE VERA LEAF; POLYSORBATE 60; POLYSORBATE 80; CETYL ESTERS WAX; ZINC PIDOLATE; SODIUM PYRROLIDONE CARBOXYLATE; PANTHENOL; .ALPHA.-TOCOPHEROL ACETATE; GLYCERYL MONOSTEARATE; SILICON DIOXIDE; HYALURONATE SODIUM; PHYTATE SODIUM; POTASSIUM CETYL PHOSPHATE; XANTHAN GUM; SODIUM HYDROXIDE; PHENOXYETHANOL; ETHYLHEXYLGLYCERIN

TRIDERMA Protect & Heal Non-Greasy Barrier

Active ingredients

Allantoin 1.5%

Dimethicone 2%

Purpose

Skin Protectant

INDICATIONS AND USAGE

Uses •helps treat and prevent diaper rash. Protects chafed skin/minor skin irritation due to/associated with diaper rash •helps protect from/seal out wetness •temporarily protect and helps relieve chafed, chapped, or cracked skin

WARNINGS

Warnings For external use only. Do not use •on deep puncture wounds •on infections •on lacerations. When using this product •do not get into eyes Stop use and ask a doctor if •condition worsens or does not improve within 7 days.

Keep out of reach of children. If swallowed get medical help or contact a Poison Control Center right away.

DOSAGE AND ADMINISTRATION

Directions •gently clean the irritated area before use. Then apply a generous layer of cream. It can be left on thick or rubbed into skin. Use as many times a day as necessary until healed. For continuous protection and healthy skin, use daily or as needed.

Other information •store at room temperature •use on infants, children or adults

INACTIVE INGREDIENT

Inactive ingredients: water, butyrospermum parkii (shea) butter, glycerin, glyceryl stearate SE, cera alba (beeswax), cetearyl alcohol, carthamus tinctorius (safflower) seed oil, avena sativa (oat) kernel flour, aloe barbadensis leaf juice*, polysorbate 60, polysorbate 80, cetyl esters, zinc PCA, sodium PCA, panthenol (pro-vitamin B-5), tocopheryl acetate (vitamin E), glyceryl stearate, silica, sodium hyaluronate, sodium phytate, potassium cetyl phosphate, xanthan gum, sodium hydroxide, phenoxyethanol, ethylhexylglycerin.*Certified Organic Ingredient - Mayacert Certifier

QUESTIONS

Questions? 1-800-279-7282 M-F 8am-4pm PST

Helps treat and prevent diaper rash
Temporarily protects and helps relieve chafed, chapped, or cracked skin

AP4® BOTANICAL

ALOE VERA COMPLEX

Allantoin & Dimenthicone

Dist. by: Genuine Virgin Aloe Corp., Corona, CA 92879 Made in USA